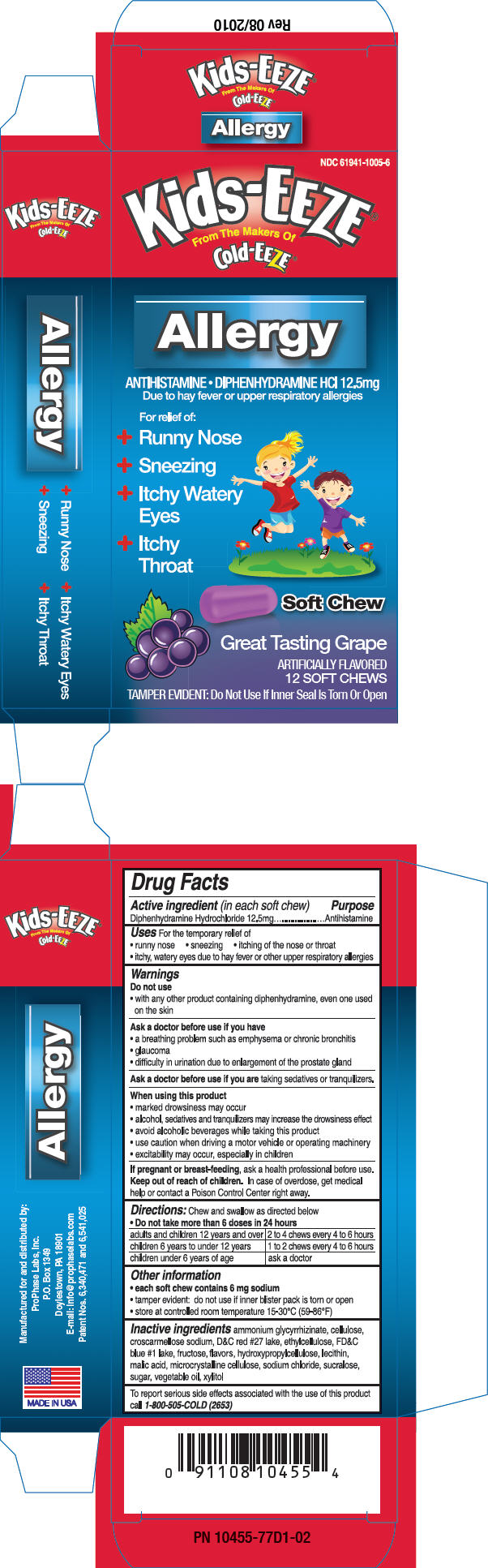 DRUG LABEL: Kids-EEZE 
NDC: 61941-1005 | Form: TABLET, ORALLY DISINTEGRATING
Manufacturer: ProPhase Labs, Inc.
Category: otc | Type: HUMAN OTC DRUG LABEL
Date: 20110401

ACTIVE INGREDIENTS: Diphenhydramine Hydrochloride 12.5 mg/1 1
INACTIVE INGREDIENTS: CROSCARMELLOSE SODIUM; ETHYLCELLULOSE (4 MPA.S); FRUCTOSE; MALIC ACID; LECITHIN, SOYBEAN; SODIUM CHLORIDE; SUCRALOSE; XYLITOL; HYDROXYPROPYL CELLULOSE

Kids-EEZE®
Allergy
Soft Chews
Great Tasting Grape

Drug Facts

Active ingredient (in each soft chew)

Diphenhydramine Hydrochloride 12.5mg

Purpose

Antihistamine

Uses

For the temporary relief of

- runny nose
- sneezing
- itching of the nose or throat
- itchy, watery eyes due to hay fever or other upper respiratory allergies

Warnings

Do not use

- with any other product containing diphenhydramine, even one used on the skin

Ask a doctor before use if you have

- a breathing problem such as emphysema or chronic bronchitis
- glaucoma
- difficulty in urination due to enlargement of the prostate gland

Ask a doctor before use if you are taking sedatives or tranquilizers.

When using this product

- marked drowsiness may occur
- alcohol, sedatives and tranquilizers may increase the drowsiness effect
- avoid alcoholic beverages while taking this product
- use caution when driving a motor vehicle or operating machinery
- excitability may occur, especially in children

PREGNANCY OR BREAST FEEDING

If pregnant or breast-feeding, ask a health professional before use.

Keep out of reach of children. In case of overdose, get medical help or contact a Poison Control Center right away.

Directions

Chew and swallow as directed below

- Do not take more than 6 doses in 24 hours

adults and children 12 years and over | 2 to 4 chews every 4 to 6 hours
children 6 years to under 12 years | 1 to 2 chews every 4 to 6 hours
children under 6 years of age | ask a doctor

Other information

- each soft chew contains 6 mg sodium
- tamper evident: do not use if inner blister pack is torn or open
- store at controlled room temperature 15-30°C (59-86°F)

Inactive ingredients

ammonium glycyrrhizinate, cellulose, croscarmellose sodium, D&C red #27 lake, ethylcellulose, FD&C blue #1 lake, fructose, flavors, hydroxypropylcellulose, lecithin, malic acid, microcrystalline cellulose, sodium chloride, sucralose, sugar, vegetable oil, xylitol

QUESTIONS

To report serious side effects associated with the use of this product call 1-800-505-COLD (2653)

PRINCIPAL DISPLAY PANEL - 12.5 mg Package

NDC 61941-1005-6

Kids-EEZE®
From The Makers Of
Cold-EEZE®

Allergy

ANTIHISTAMINE • DIPHENHYDRAMINE HCl 12.5mg
Due to hay fever or upper respiratory allergies

For relief of:

+ Runny Nose
+ Sneezing
+ Itchy Watery
  Eyes
+ Itchy
  Throat

Soft Chew

Great Tasting Grape

ARTIFICIALLY FLAVORED
12 SOFT CHEWS

TAMPER EVIDENT: Do Not Use If Inner Seal Is Torn Or Open